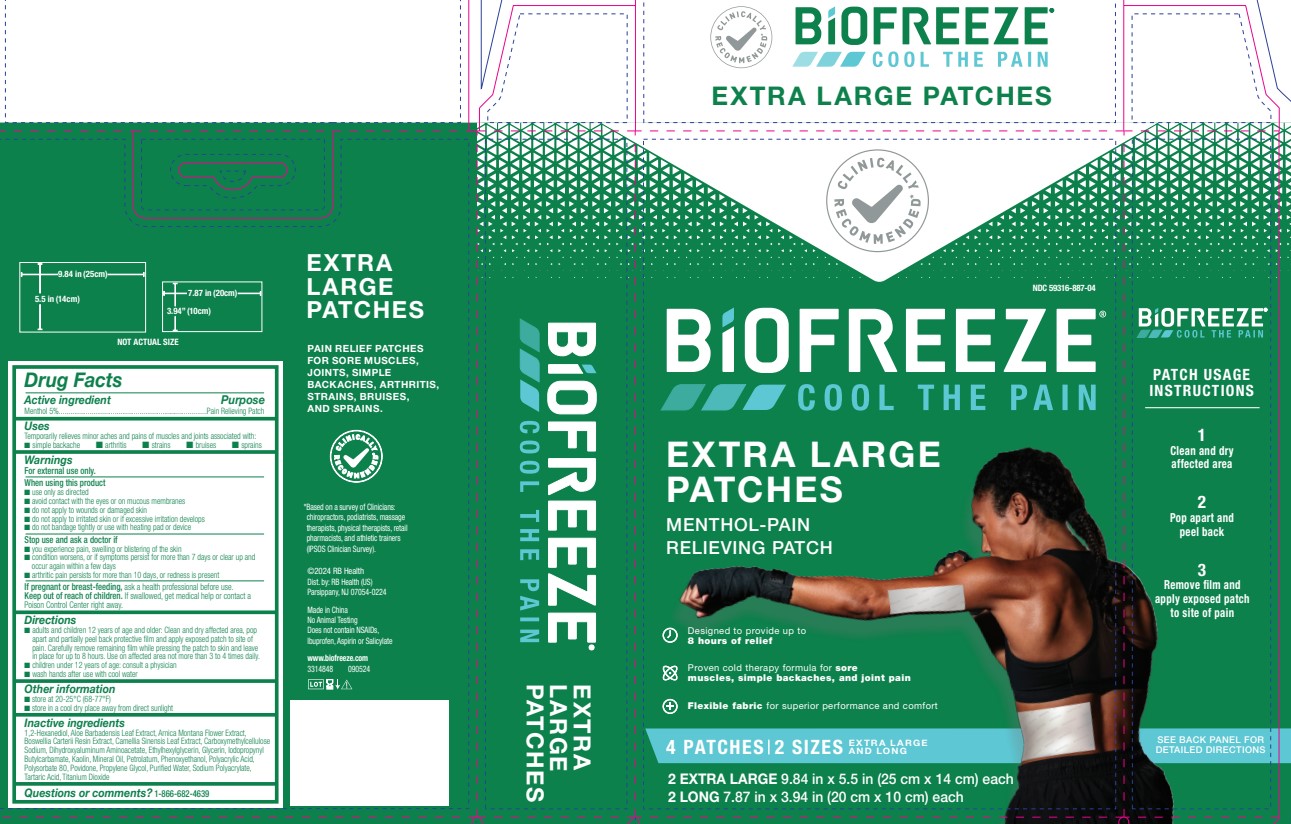 DRUG LABEL: Biofreeze
NDC: 59316-887 | Form: KIT | Route: TOPICAL
Manufacturer: RB Health (US) LLC
Category: otc | Type: HUMAN OTC DRUG LABEL
Date: 20240925

ACTIVE INGREDIENTS: MENTHOL, UNSPECIFIED FORM 0.05 g/1 g; MENTHOL, UNSPECIFIED FORM 0.05 g/1 g
INACTIVE INGREDIENTS: ALOE VERA LEAF; ARNICA MONTANA FLOWER; FRANKINCENSE; GREEN TEA LEAF; CARBOXYMETHYLCELLULOSE SODIUM, UNSPECIFIED; DIHYDROXYALUMINUM AMINOACETATE; ETHYLHEXYLGLYCERIN; GLYCERIN; IODOPROPYNYL BUTYLCARBAMATE; KAOLIN; MINERAL OIL; PHENOXYETHANOL; PETROLATUM; POLYACRYLIC ACID (450000 MW); POLYSORBATE 80; PROPYLENE GLYCOL; POVIDONE, UNSPECIFIED; SODIUM POLYACRYLATE (2500000 MW); TARTARIC ACID; TITANIUM DIOXIDE; WATER; 1,2-HEXANEDIOL; 1,2-HEXANEDIOL; ALOE VERA LEAF; ARNICA MONTANA FLOWER; FRANKINCENSE; GREEN TEA LEAF; CARBOXYMETHYLCELLULOSE SODIUM, UNSPECIFIED; DIHYDROXYALUMINUM AMINOACETATE; ETHYLHEXYLGLYCERIN; GLYCERIN; IODOPROPYNYL BUTYLCARBAMATE; KAOLIN; MINERAL OIL; PHENOXYETHANOL; PETROLATUM; POLYACRYLIC ACID (450000 MW); POLYSORBATE 80; PROPYLENE GLYCOL; POVIDONE, UNSPECIFIED; SODIUM POLYACRYLATE (2500000 MW); TARTARIC ACID; TITANIUM DIOXIDE; WATER

Biofreeze®
Menthol Patches

Drug Facts

Active ingredient

Menthol 5%

Purpose

Pain Relieving Patch

Uses

Temporarily relieves minor aches and pains of muscles and joints associated with:

- simple backache
- arthritis
- strains
- bruises
- sprains

Warnings

For external use only.

When using this product

- use only as directed
- avoid contact with the eyes or on mucous membranes
- do not apply to wounds or damaged skin
- do not apply to irritated skin or if excessive irritation develops
- do not bandage tightly or use with heating pad or device

Stop use and ask a doctor if

- you experience pain, swelling or blistering of the skin
- condition worsens, or if symptoms persist for more than 7 days or clear up and occur again within a few days
- arthritic pain persists for more than 10 days, or redness is present

PREGNANCY OR BREAST FEEDING

If pregnant or breast-feeding,ask a health professional before use.

Keep out of reach of children.If swallowed, get medical help or contact a Poison Control Center right away.

Directions

- adults and children 12 years of age and older: Clean and dry affected area, pop apart and partially peel back protective ﬁlm and apply exposed patch to site of pain. Carefully remove remaining ﬁlm while pressing the patch to skin and leave in place for up to 8 hours. Use on affected area not more than 3 to 4 times daily.
- children under 12 years of age: consult a physician
- wash hands after use with cool water

Other information

- store at 20-25°C (68-77°F)
- store in a cool dry place away from direct sunlight

Inactive ingredients

1,2-Hexanediol, Aloe Barbadensis Leaf Extract, Arnica Montana Flower Extract, Boswellia Carterii Resin Extract, Camellia Sinensis Leaf Extract, Carboxymethylcellulose Sodium, Dihydroxyaluminum Aminoacetate, Ethylhexylglycerin, Glycerin, Iodopropynyl Butylcarbamate, Kaolin, Mineral Oil, Petrolatum, Phenoxyethanol, Polyacrylic Acid, Polysorbate 80, Povidone, Propylene Glycol, Purified Water, Sodium Polyacrylate, Tartaric Acid, Titanium Dioxide

Questions or comments?

1-800-246-3733

Dist. by: RB Health (US)
Parsippany, NJ 07054-0224

PRINCIPAL DISPLAY PANEL - Kit Carton

CLINICALLY
RECOMMENDED*

NDC 59316-887-04

BiOFREEZE®
COOL THE PAIN

EXTRA LARGE
PATCHES

MENTHOL-PAIN
RELIEVING PATCH

Designed to provide up to
8 hours of long lasting pain relief

Proven cold therapy formula for sore
muscles, simple backaches, and joint pain

Flexible fabric for superior performance and comfort

4 PATCHES | 2 SIZES
EXTRA LARGE
AND LONG

2 EXTRA LARGE 9.84 in x 5.5 in (25 cm x 14 cm) each
2 LONG 7.87 in x 3.94 in (20 cm x 10 cm) each